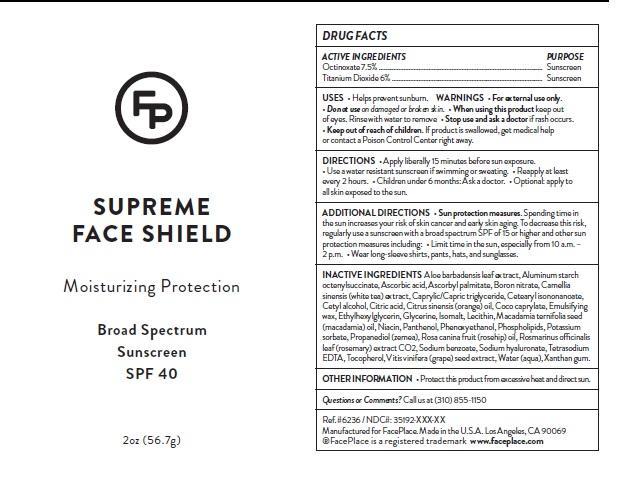 DRUG LABEL: Umbrella Sunscreen
NDC: 35192-013 | Form: LOTION
Manufacturer: CA-BOTANA INTERNATIONAL
Category: otc | Type: HUMAN OTC DRUG LABEL
Date: 20131010

ACTIVE INGREDIENTS: TITANIUM DIOXIDE 3 g/50 g; OCTINOXATE 3.75 g/50 g
INACTIVE INGREDIENTS: ALOE VERA LEAF; ALUMINUM STARCH OCTENYLSUCCINATE; ASCORBIC ACID; ASCORBYL PALMITATE; BORON NITRIDE; CETOSTEARYL ALCOHOL; CETEARYL ISONONANOATE; CITRIC ACID MONOHYDRATE; CAPRYLIC/CAPRIC MONO/DIGLYCERIDES; ETHYLHEXYLGLYCERIN; GLYCERIN; SUNFLOWER OIL; ISOMALT; MACADAMIA OIL; NIACIN; PANTHENOL; PHENOXYETHANOL; LECITHIN, SOYBEAN; POTASSIUM SORBATE; PROPANEDIOL; ROSA MOSCHATA OIL; ROSEMARY; SODIUM BENZOATE; HYALURONATE SODIUM; TETRASODIUM IMINODISUCCINATE; TOCOPHEROL; GRAPE SEED OIL; WATER

6236 Umbrella Sunscreen Lotion

WARNINGS

For external use only. Do not use on damaged or broken skin. When using this product keep out of eyes. Rinse with water to remove. Stop use and ask a doctor if rash occurs. Keep out of reach of children. If product is swallowed, get medical help or contact a poison control center right away.

DOSAGE AND ADMINISTRATION

Helps prevent sunburn. If used as directed with other sun protection measured decreases the risk of skin cancer and early skin aging caused by the sun. Apply liberally 15 minutes before sun exposure. Use a water resistant sunscreen if swimming or sweating. Reapply: at least 2 hours. Children under 6 months: Ask a doctor. Sun protection measurements. Spending time in the sun increases your risk of skin cancer and early skin aging. To decrease this risk, regularly use a sunscreen with a broad spectrum SPF of 15 or higher and other sun protection measures including: limit time in the sun, especially from 10 a.m - 2 p.m. Wear long-sleeve shirts, pants, hats, and sunglasses. Protect this product from excessive heat and direct sun

INACTIVE INGREDIENT

ALOE VERA LEAF, ALUMINUM STARCH OCTENYLSUCCINATE, ASCORBIC ACID, ASCORBYL PALMITATE, BORON NITRIDE, CETOSTEARYL ALCOHOL, CETEARYL ISONONANOATE, CITRIC ACID MONOHYDRATE, CAPRYLIC/CAPRIC MONO/DIGLYCERIDES, ETHYLHEXYLGLYCERIN, GLYCERIN, SUNFLOWER OIL, ISOMALT, LECITHIN SOYBEAN, MACADAMIA OIL, NIACIN, PANTHENOL, PHENOXYETHANOL, LECITHIN SOYBEAN, POTASSIUM SORBATE, PROPANEDIOL, ROSA MOSCHATA OIL, ROSEMARY, SODIUM BENZOATE, HYALURONATE SODIUM, TETRASODIUM IMINODISUCCINATE, TOCOPHEROL, GRAPE SEED OIL, WATER

PURPOSE

Sunscreen

ACTIVE INGREDIENT

Titanium Dioxide, Octinoxate

KEEP OUT OF REACH OF CHILDREN

For external use only.
Avoid contact with eyes.
Keep out of reach of children.
Do not apply to open wounds.
STOP USE AND ask a doctor if condition worsens or
symptoms persist for more than seven days, discontinue
use of the product.

INDICATIONS AND USAGE

Helps prevent sunburn. If used as directed with other sun protection measured decreases the risk of skin cancer and early skin aging caused by the sun. Apply liberally 15 minutes before sun exposure. Use a water resistant sunscreen if swimming or sweating. Reapply: at least 2 hours. Children under 6 months: Ask a doctor. Sun protection measurements. Spending time in the sun increases your risk of skin cancer and early skin aging. To decrease this risk, regularly use a sunscreen with a broad spectrum SPF of 15 or higher and other sun protection measures including: limit time in the sun, especially from 10 a.m - 2 p.m. Wear long-sleeve shirts, pants, hats, and sunglasses. Protect this product from excessive heat and direct sun

PACKAGE LABEL

Enter section text here